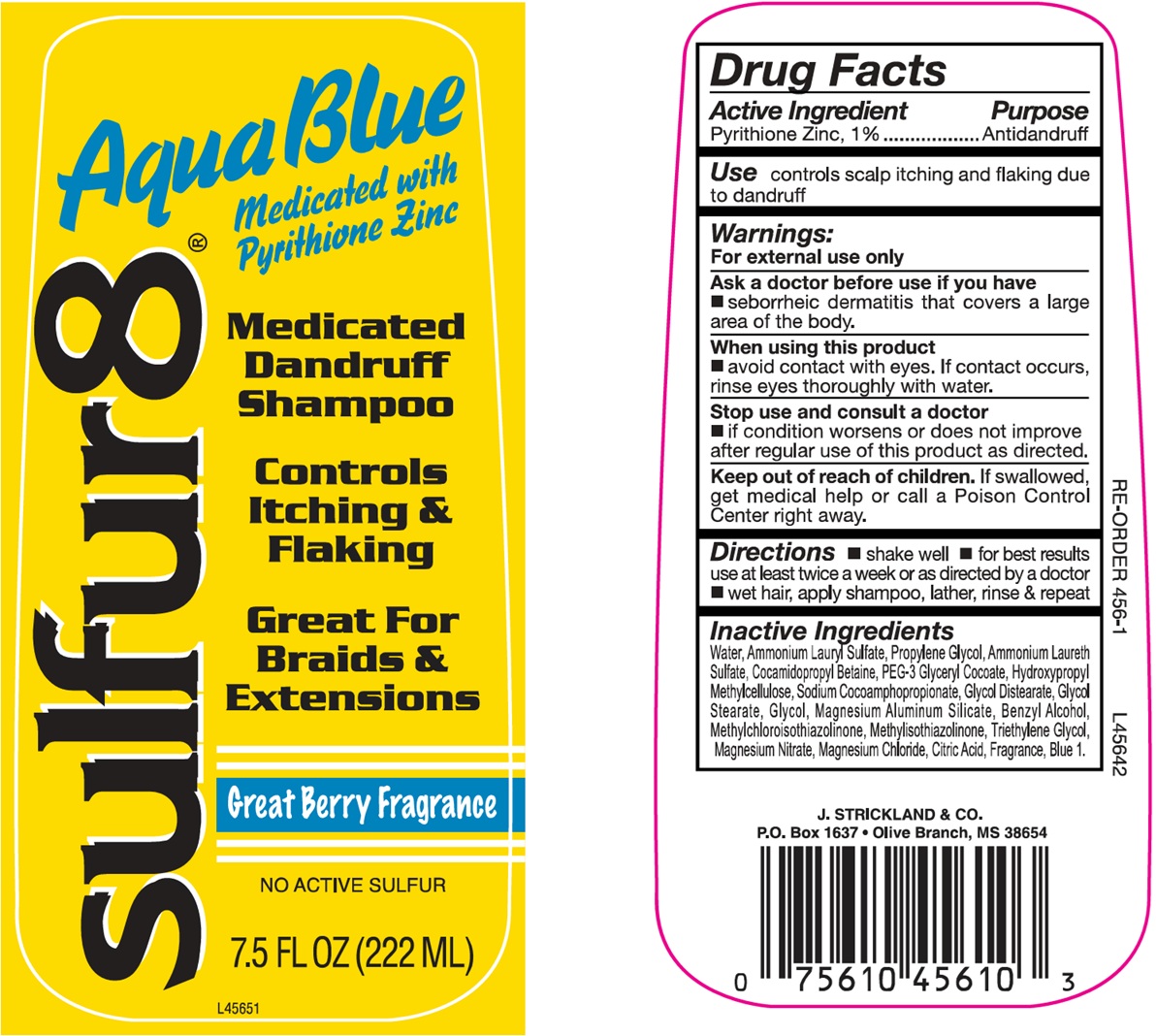 DRUG LABEL: Sulfur 8 Aqua Blue
NDC: 12022-024 | Form: SHAMPOO, SUSPENSION
Manufacturer: J. Strickland & Co.
Category: otc | Type: HUMAN OTC DRUG LABEL
Date: 20251107

ACTIVE INGREDIENTS: PYRITHIONE ZINC 10 mg/1 mL
INACTIVE INGREDIENTS: WATER; AMMONIUM LAURYL SULFATE; COCAMIDOPROPYL BETAINE; HYPROMELLOSE, UNSPECIFIED; GLYCOL STEARATE; MAGNESIUM ALUMINUM SILICATE; BENZYL ALCOHOL; METHYLCHLOROISOTHIAZOLINONE; METHYLISOTHIAZOLINONE; TRIETHYLENE GLYCOL; MAGNESIUM NITRATE; MAGNESIUM CHLORIDE; CITRIC ACID MONOHYDRATE; FD&C BLUE NO. 1

Sulfur 8 Aqua Blue Shampoo

Active Ingredients

Pyrithione Zinc, 1%

Purpose

Antidandruff

Use:

controls scalp itching and flaking due to dandruff

Warnings:

For external use only

Ask a doctor before use if you have

- seborrheic dermatitis that covers a large area of the body.

When using this product

- avoid contact with eyes. If contact occurs, rinse eyes thoroughly with water.

Stop use and consult a doctor if

- if conditions worsens or does not improve after regular use of this product as directed.

Keep out of reach of children

If swallowed, get medical help or call a Poison Control Center right away.

Directions

- shake well
- for best results, use twice a week or as directed by a doctor
- wet hair, apply shampoo, lather, rinse & repeat

Inactive Ingredients

Water, Ammonium Lauryl Sulfate, Propylene Glycol, Ammonium Laureth Sulfate, Cocamidopropyl Betaine, PEG-3 Glyceryl Cocate, Hydroxypropyl Methylcellulose, Sodium Cocoamphopropiante, Glycol Distearate, Glycol Stearate, Glycol, Magnesium Aluminum Silicate, Benzyl Alcohol, Methylchloroisothiazolinone, Methylisothiazolinone, Triethylene Glycol, Magnesium Nitrate, Magnesium Chloride, Citric Acid, Fragrance, Blue 1